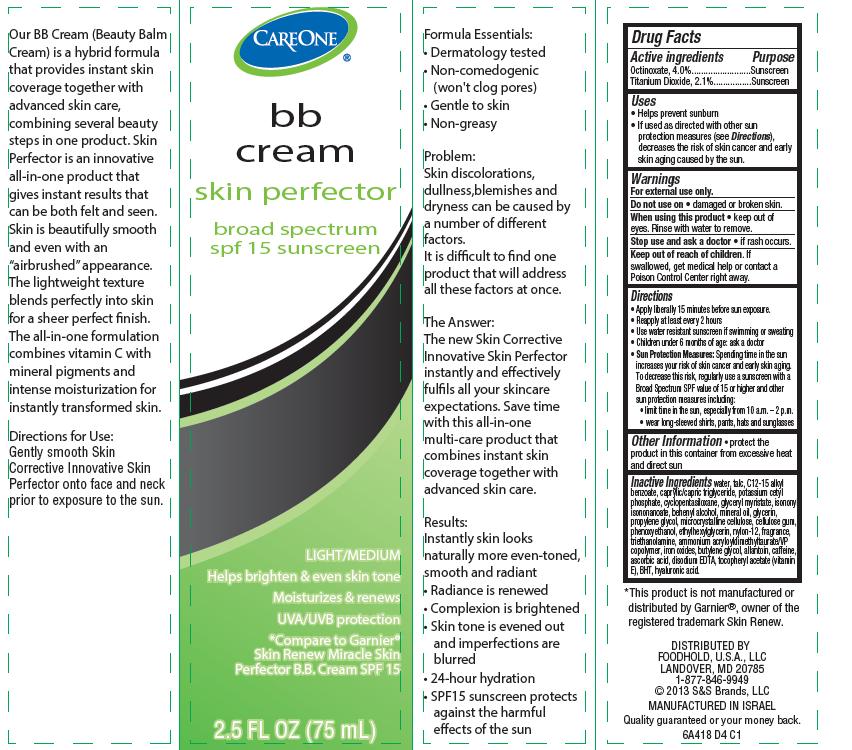 DRUG LABEL: Skin Corrective Innovative Skin Perfector BB Broad Spectrum SPF15 Sunscreen Light Medium
NDC: 41520-418 | Form: CREAM
Manufacturer: American Sales Company
Category: otc | Type: HUMAN OTC DRUG LABEL
Date: 20130926

ACTIVE INGREDIENTS: TITANIUM DIOXIDE 2.1 g/100 mL; OCTINOXATE 4 g/100 mL
INACTIVE INGREDIENTS: TALC; WATER; ALKYL (C12-15) BENZOATE; TRICAPRIN; POTASSIUM CETYL PHOSPHATE; CYCLOMETHICONE 5; GLYCERYL MYRISTATE; ISONONYL ISONONANOATE; DOCOSANOL; MINERAL OIL; GLYCERIN; PROPYLENE GLYCOL; CELLULOSE, MICROCRYSTALLINE; CARBOXYMETHYLCELLULOSE SODIUM; PHENOXYETHANOL; ETHYLHEXYLGLYCERIN; NYLON-12; TROLAMINE; AMMONIUM ACRYLOYLDIMETHYLTAURATE/VP COPOLYMER; FERRIC OXIDE RED; BUTYLENE GLYCOL; ALLANTOIN; CAFFEINE; ASCORBIC ACID; EDETATE DISODIUM; .ALPHA.-TOCOPHEROL ACETATE; BUTYLATED HYDROXYTOLUENE; HYALURONIC ACID

CareOne Skin Corrective Innovative Skin Perfector BB Broad Spectrum SPF15 Sunscreen

Active ingredient

Octinoxate 4.0%
Titanium Dioxide 2.1%

Purpose

Sunscreen

Uses

- helps prevent sunburn
- If used as directed with other sun protection measures (see Directions), decreases the risk of skin cancer and early skin aging caused by the sun

Warnings

For external use only.

Do not use on

- damaged or broken skin.

When using this product

- keep out of eyes. Rinse with water to remove.

Stop use and ask a doctor

- if rash occurs.

Keep Out of Reach of Children

If swallowed, get medical help or contact a Poison Control Center right away.

Directions

- Apply liberally 15 minutes before sun exposure.
- Reapply at least every 2 hours.
- Use water-resistant sunscreen if swimming or sweating.
- Children under 6 months: ask a doctor.
- Sun Protection Measures: Spending time in the sun increases your risk of skin cancer and early skin aging. To decrease this risk regularly use a sunscreen with a Broad Spectrum SPF value of 15 or higher and other sun protection measures including:
  - limit time in the sun, especially from 10 a.m. - 2 p.m.
  - wear long-sleeved shirts, pants, hats and sunglasses.

Other Information

- protect the product in this container from excessive heat and direct sun

Inactive Ingredients

water, talc, C12-15 alkyl benzoate, caprylic/capric triglyceride, potassium cetyl phosphate, cyclopentasiloxane, glyceryl myristate, isononyl isononanoate, behenyl alcohol, mineral oil, glycerin, propylene glycol, microcrystalline cellulose, cellulose gum, phenoxyethanol, ethylhexylglycerin, nylon-12, fragance, triethanolamine, ammonium acryloyldimethyltaurate/VP copolymer, iron oxides, butylene glycol, allantoin, caffeine, ascorbic acid, disodium EDTA, tocopheryl actetate (vitamin E), BHT, hyaluronic acid.

Package/Label Principal Display Panel

CAREONE® bb cream skin perfector
broad spectrum
spf 15 sunscreen

LIGHT/MEDIUM

Helps brighten & even skin tone

Moisturizes & renews

UVA/UVB protection

Compare to Garnier® Skin Renew Miracle Skin Protector B.B. Cream SPF 15

2.5 FL OZ (75 mL)

Our BB Cream (Beauty Balm Cream) is a hybrid formula that provides instant skin coverage together with advanced skin care, combining several beauty steps in one product. Skin Perfector is an innovative all-in-one product that gives instant results that can be both felt and seen. Skin is beautifully smooth and even with an "airbrushed" appearance. The lightweight texture blends perfectly into skin for a sheer perfect finish. The all-in-one formulation combines vitamin C with mineral pigments and intense moisturization for instantly transformed skin.

Directions for Use:
Gently smooth Skin Corrective Innovative Skin Perfector onto face and neck prior to exposure to the sun.

Formula Essentials:

- Dermatology tested
- Non-comedogenic (won't clog pores)
- Gentle to skin
- Non-greasy

Problem:

Skin discolorations, dullness, blemishes and dryness can be caused by a number of different factors.
It is difficult to find one product that will address all these factors at once.

The Answer:
The new Skin Corrective Innovative Skin Perfector instantly and effectively fulfils all your skincare expectations. Save time with this all-in-one multi-care product that combines instant skin coverage together with advanced skin care.

Results:
Instantly skin looks naturally more even-toned, smooth and radiant

- Radiance is renewed
- Complexion is brightened
- Skin tone is evened out and imprefections are blurred
- 24-hour hydration
- SPF15 sunscreen protects against the harmful effects of the sun

*This product is not manufactured or distributed by Garnier®, owner of the registered trademark Skin Renew.

DISTRIBUTED BY FOODHOLD, U.S.A., LLC
LANDOVER, MD 20785
1-877-846-9949
© 2013 S&S Brands, LLC
MANUFACTURED IN ISRAEL

Quality guaranteed or your money back.

6A418 D4 C1

Carton Label